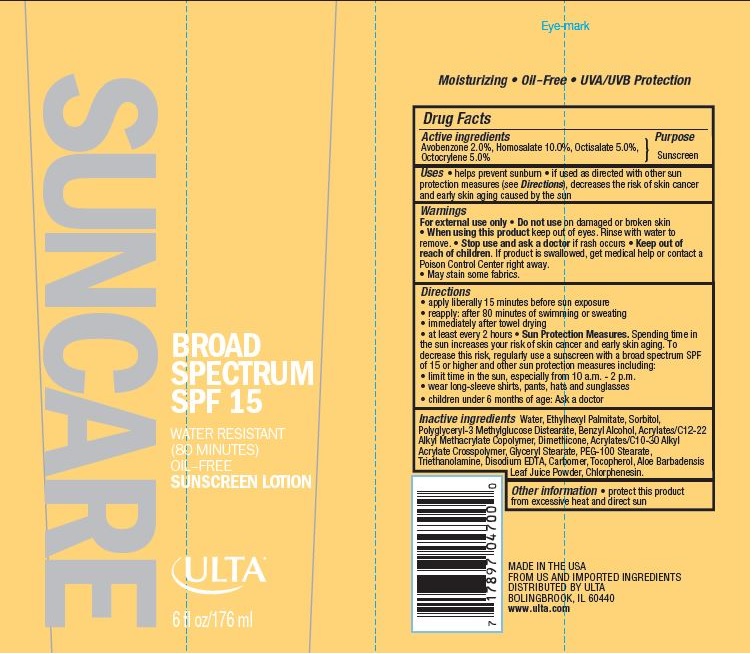 DRUG LABEL: ULTA SUNSCREEN SPF 15
NDC: 62296-8210 | Form: LOTION
Manufacturer: Ulta
Category: otc | Type: HUMAN OTC DRUG LABEL
Date: 20160125

ACTIVE INGREDIENTS: AVOBENZONE 2 g/100 g; HOMOSALATE 10 g/100 g; OCTISALATE 5 g/100 g; OCTOCRYLENE 5 g/100 g
INACTIVE INGREDIENTS: WATER; ETHYLHEXYL PALMITATE; SORBITOL; BENZYL ALCOHOL; DIMETHICONE; CHLORPHENESIN; GLYCERYL MONOSTEARATE; PEG-100 STEARATE; CARBOXYPOLYMETHYLENE; TOCOPHEROL; ALOE VERA LEAF

Drug Facts

Active Ingredients

AVOBENZONE 2.0%, HOMOSALATE 10.0%, OCTISALATE 5.0%, OCTOCRYLENE 5.0%

Purpose

Sunscreen

Uses

- helps prevent sunburn
- If used as directed with other sun protection measures (see Directions), decreases the risk of skin cancer and early skin aging caused by the sun

Warnings

For external use only

Do not use

on damaged or broken skin

When using this product

keep out of eyes. Rinse with water to remove.

Stop use and ask a doctor

if rash occurs.

Keep out of reach of children.

If product is swallowed, get medical help or contact a Poison Control center right away.

- May stain some fabrics

Directions

- apply liberally 15 minutes before sun exposure
- reapply: after 80 minutes of swimming or sweating
- immediately after towel drying
- at least every 2 hours
- Sun Protection Measures: Spending time in the sun increases your risk of skin cancer and early skin aging. To decrease this risk, regularly use a sunscreen with a broad spectrum SPF of 15 or higher and other sun protection measures including:
- limit time in the sun, especially from 10 a.m. - 2 p.m.
- wear long-sleeve shirts, pants, hats and sunglasses
- children under 6 months of age: Ask a doctor

Inactive Ingredients

Water, Ethylhexyl Palmitate, Sorbitol, Polyglyceryl-3 Methylglucose Distearate, Benzyl Alcohol, Dimethicone, Acrylates/C10-30 Alkyl Acrylate Crosspolymer, Chlorphenesin, Acrylates/C12-22 Alkyl Methacrylate Copolymer, Glyceryl Stearate, PEG-100 Stearate, Triethanolamine, Disodium EDTA, Carbomer, Tocopherol, Aloe Barbadensis Leaf Juice Powder.

Other information:

protect this product from excessive heat and direct sun.

Principal Display Panel

62296-8210-4

SUNCARE
BROAD SPECTRUM SPF 15
WATER RESISTANT

(80 MINUTES)

OIL-FREE

SUNSCREEN LOTION
ULTA

6 fl oz/176 ml